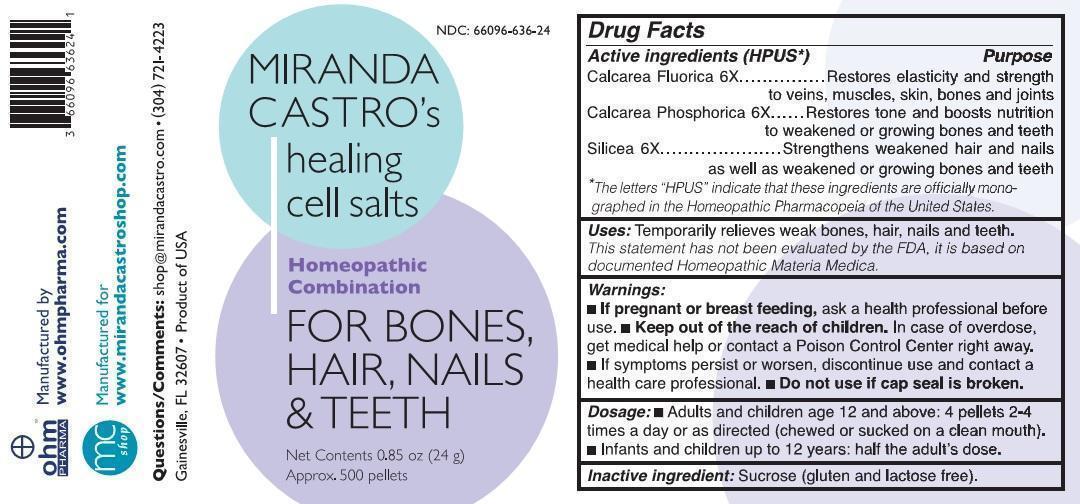 DRUG LABEL: Miranda Castros healing cell salts for bones, hair, nails and teeth



NDC: 66096-636 | Form: PELLET
Manufacturer: OHM PHARMA INC.
Category: homeopathic | Type: HUMAN OTC DRUG LABEL
Date: 20221202

ACTIVE INGREDIENTS: CALCIUM FLUORIDE 6 [hp_X]/1 1; TRIBASIC CALCIUM PHOSPHATE 6 [hp_X]/1 1; SILICON DIOXIDE 6 [hp_X]/1 1
INACTIVE INGREDIENTS: SUCROSE

MIRANDA CASTRO's healing cell salts Homeopathic Combination FOR BONES, HAIR, NAILS & TEETH

Active ingredients (HPUS*) | Purpose
Calcarea Fluorica 6X | Restores elasticity and strength to veins, muscles, skin, bones and joints
Calcarea Phosphorica 6X | Restores tone and boosts nutrition to weakened or growing bones and teeth
Silicea 6X | Strengthens weakened hair and nails as well as weakened or growing bones and teeth

*The letters "HPUS" indicate that these ingredients are officially monographed in the Homeopathic Pharmacopeia of the United States.

INDICATIONS AND USAGE

Uses: Temporarily relieves weak bones, hair, nails and teeth.

This statement has not been evaluated by the FDA, it is based on documented Homeopathic Materia Medica.

Warnings:

- If pregnant or breast-feeding, ask a health care professional before use.
- Keep out of the reach of children. In case of overdose, get medical help or contact a Poison Control Center right away.
- If symptoms persist or worsen, discontinue use and contact a health care professional.
- Do not use if cap seal is broken.

Keep out of the reach of children.

Dosage:

- Adults and children age 12 and above: 4 pellets 2-4 times a day or as directed (chewed or sucked on a clean mouth).
- Infants and children up to 12 years: half the adult's dose.

Inactive ingredient: Sucrose (gluten and lactose free).

Questions/Comments: shop@mirandacastro.com

(304) 721-4223

Gainesville, FL 32607

Product of USA

Manufactured by www.ohmpharma.com

Manufactured for www.mirandacastroshop.com

PURPOSE

Homeopathic Combination FOR BONES, HAIR, NAILS and TEETH

PACKAGE LABEL

NDC: 66096-636-24

MIRANDA CASTRO's healing cell salts Homeopathic Combination FOR BONES, HAIR, NAILS and TEETH

Net Contents 0.85oz (24 g)

Approx. 500 pellets